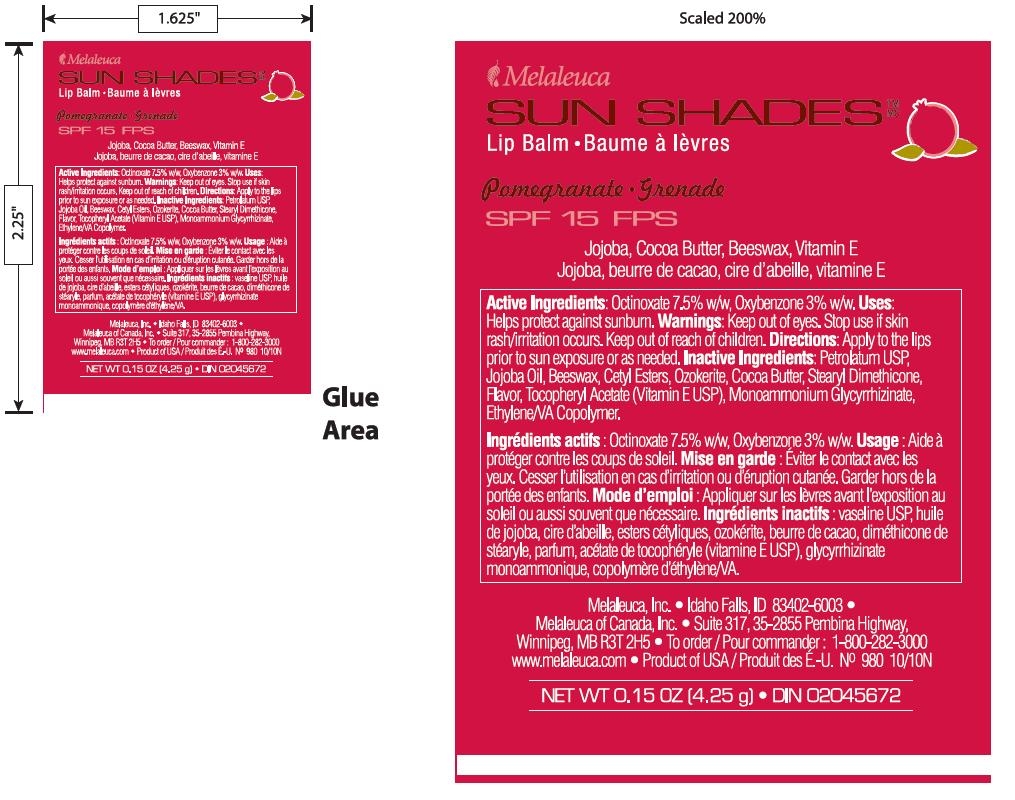 DRUG LABEL: Sun Shades Lip Balm 
NDC: 54473-168 | Form: STICK
Manufacturer: Melaleuca, Inc.
Category: otc | Type: HUMAN OTC DRUG LABEL
Date: 20101215

ACTIVE INGREDIENTS: Octinoxate 75 mg/1 g; Oxybenzone 30 mg/1 g
INACTIVE INGREDIENTS: Petrolatum; Jojoba Oil; Yellow Wax; Cetyl Esters Wax; Ceresin; Cocoa Butter; Vitamin E Acetate; Glycyrrhizin, Ammoniated; ETHYLENE-VINYL ACETATE COPOLYMER (40% VINYL ACETATE)

Drug Facts

ACTIVE INGREDIENT

Active Ingredients: Octinoxate 7.5% w/w, Oxybenzone 3% w/w.

PURPOSE

Uses: Helps protect against sunburn.

WARNINGS

Warnings: Keep out of eyes. Stop use if skin rash/irritation occurs. Keep out of reach of children.

WHEN USING

Directions: Apply to the lips prior to sun exposure or as needed.

INACTIVE INGREDIENT

Inactive Ingredients: Petrolatum USP, Jojoba Oil, Beeswax, Cetyl Esters, Ozokerite, Cocoa Butter, Stearyl Dimethicone, Flavor, Tocopheryl Acetate (Vitamin E USP), Monoammonium Glycyrrhizinate, Ethylene/VA Copolymer.

image of label